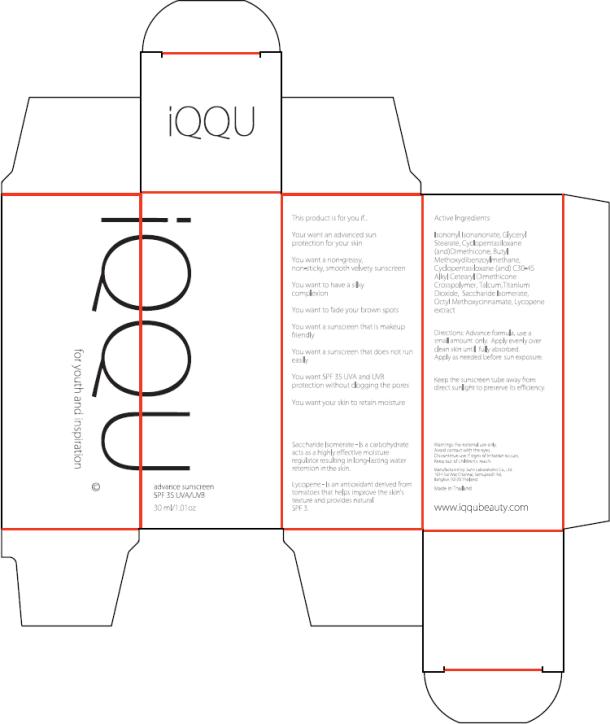 DRUG LABEL: IQQU Advance Sunscreen
NDC: 50403-999 | Form: LOTION
Manufacturer: IQQU USA Co.
Category: otc | Type: HUMAN OTC DRUG LABEL
Date: 20100207

ACTIVE INGREDIENTS: DIMETHICONE 25 g/1 mL; AVOBENZONE 22 g/1 mL; TITANIUM DIOXIDE 40 g/1 mL; OCTINOXATE 50 g/1 mL
INACTIVE INGREDIENTS: GLYCERYL MONOSTEARATE

Advance Sunscreen

IQQU
Advance Sunscreen
SPF 35 UVA/UVB

Active Ingredient

Dimethicone, Butyl Methoxydibenzoylmethane, Titanium Dioxide, Octyl Methoxycinnamate.

Directions

Advance formula, use a small amount only. Apply evenly over clean skin until fully absorbed. Apply as needed before sun exposure.

Keep the sunscreen tube away from direct sunlight to preserve its efficiency.

Warnings

For external use only. Avoid contact with the eyes. Discontinue use if signs of irritation occurs. Keep out of children’s reach.

Inactive Ingredients

Isononyl Isonanonate, Glyceryl Stearate, Cyclopentasiloxane (and) Dimethicone, Cyclopentasiloxane (and) C30-45 Alkyl Cetearyl Dimethicone Crosspolymer, Talcum

Manufactured by: June Laboratories Co., Ltd.
1014 Soi Wat Channai, Sathupradit Rd,
Bangkok 10120 Thailand.

Made in Thailand

www.iqqubeauty.com

PRINCIPAL DISPLAY PANEL

Package Label – 30 mL

IQQU Advance Sunscreen

SPF 35 UVA/UVB

30 mL /1.01 oz